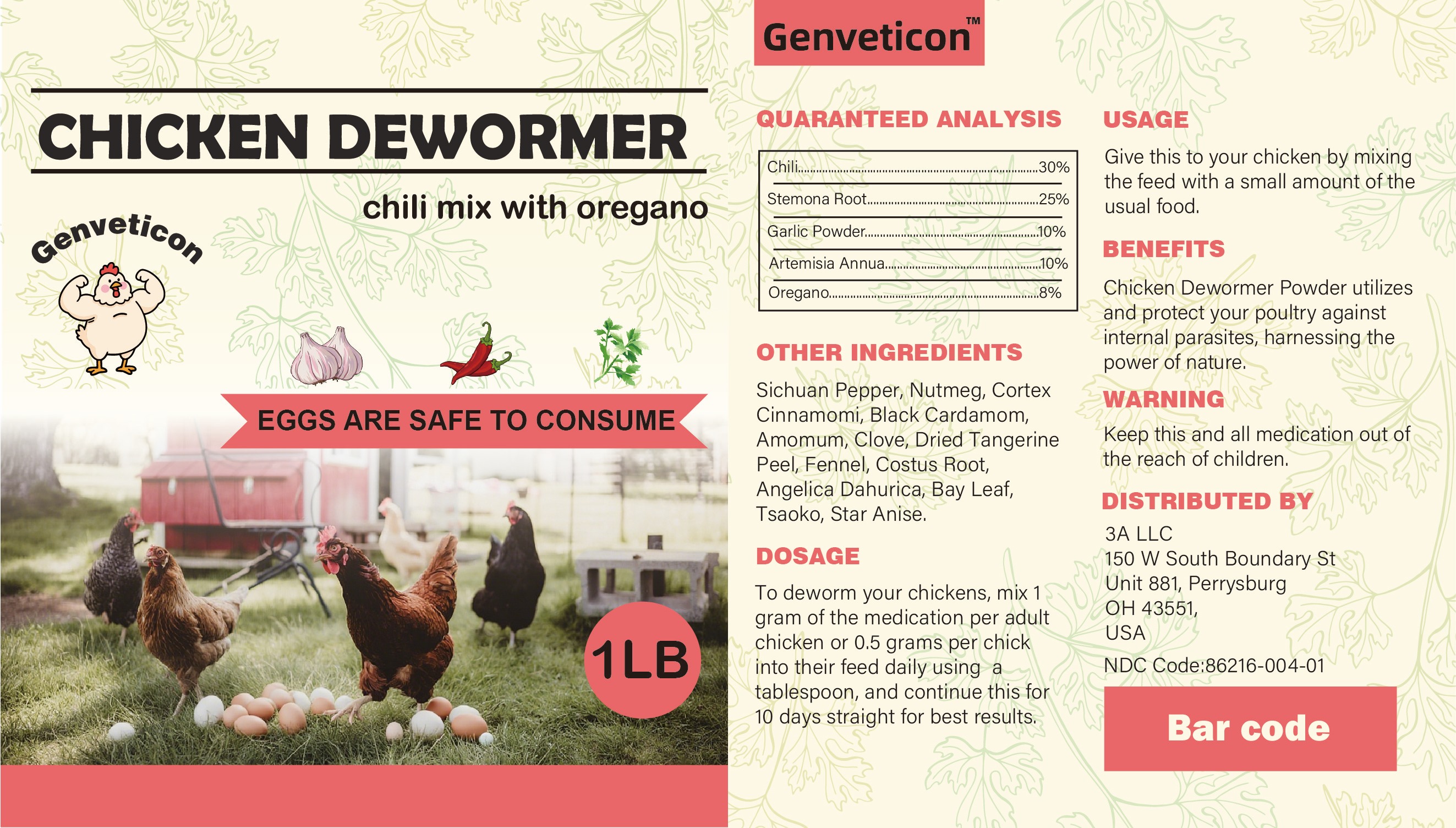 DRUG LABEL: Chicken dewormer powder
NDC: 86216-004 | Form: POWDER
Manufacturer: Pet Professional inc.
Category: animal | Type: OTC ANIMAL DRUG LABEL
Date: 20251115

ACTIVE INGREDIENTS: GARLIC 100 mg/1 g; ARTEMISIA ANNUA WHOLE 100 mg/1 g; OREGANO 80 mg/1 g

genveticon chicken dewormer powder

Usage

Mix the recommended dosage with feed using the tablespoon, One small tablespoon is enough for four chickens.Feed once daily.